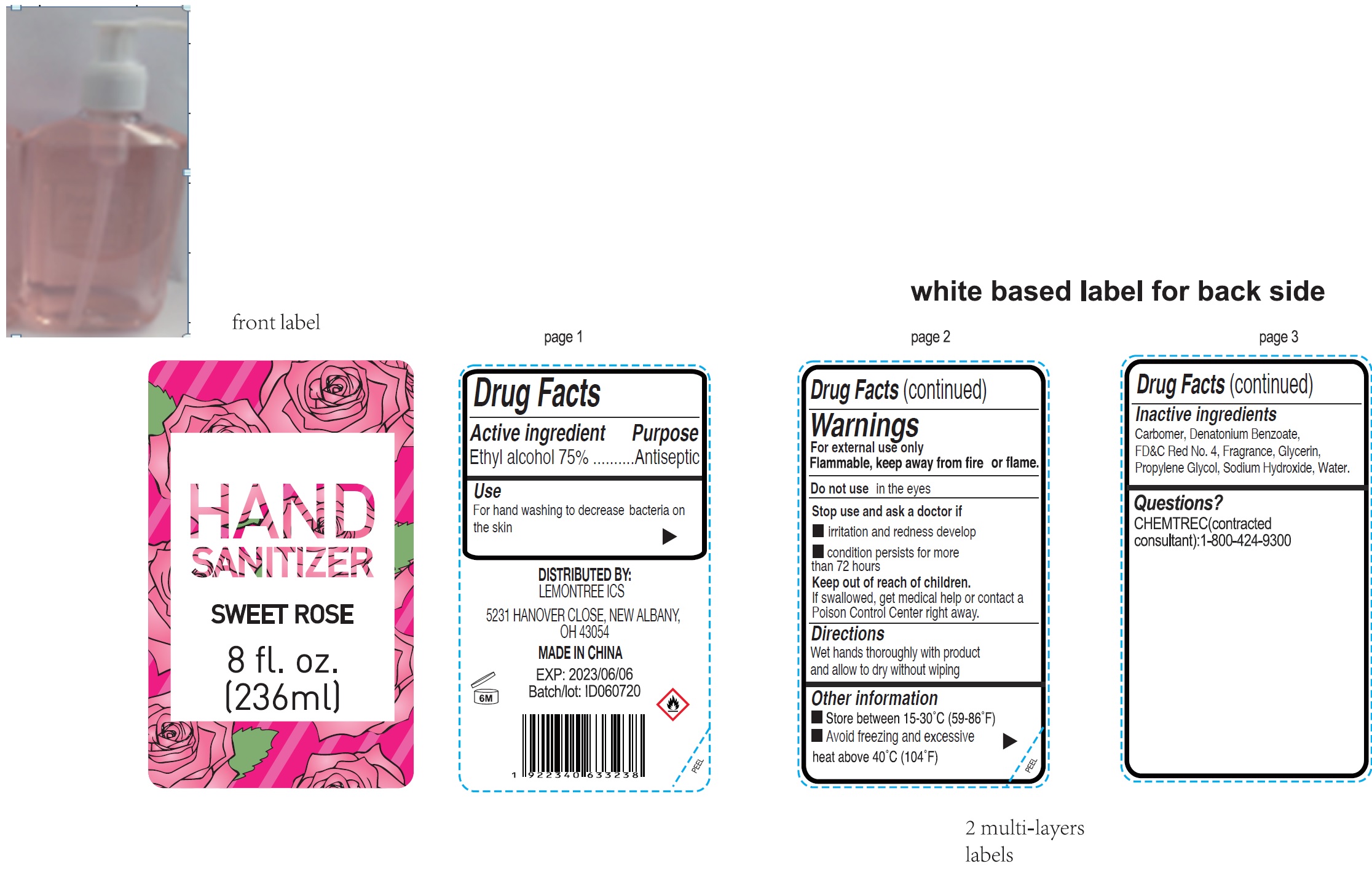 DRUG LABEL: Hand Sanitizer Sweet Rose
NDC: 79834-113 | Form: GEL
Manufacturer: Lemontree ICS
Category: otc | Type: HUMAN OTC DRUG LABEL
Date: 20200810

ACTIVE INGREDIENTS: ALCOHOL 0.75 mL/1 mL
INACTIVE INGREDIENTS: CARBOMER HOMOPOLYMER, UNSPECIFIED TYPE; DENATONIUM BENZOATE; FD&C RED NO. 4; GLYCERIN; PROPYLENE GLYCOL; SODIUM HYDROXIDE; WATER

Hand Sanitizer, Sweet Rose

Active ingredient

Ethyl alcohol 75%

Purpose

Antiseptic

Use

For hand washing to decrease bacteria on the skin

Warnings

For external use only

Flammable, keep away from fire or flame

Do not use

in the eyes

Stop use and ask a doctor if

- irritation and redness develop
- condition persists for more than 72 hours

Keep out of reach of children.

If swallowed, get medical help or contact a Poison Control Center right away.

Directions

Wet hands thoroughly with product and allow to dry without wiping

Other information

- Store between 15-30°C (59-86°F)
- Avoid freezing and excessive heat above 40°C (104°F)

Inactive ingredients

Carbomer, Denatonium Benzoate, FD&C Red No. 4, Fragrance, Glycerin, Propylene Glycol, Sodium Hydroxide, Water.

Questions?

CHEMTREC(contracted consultant):1-800-424-9300